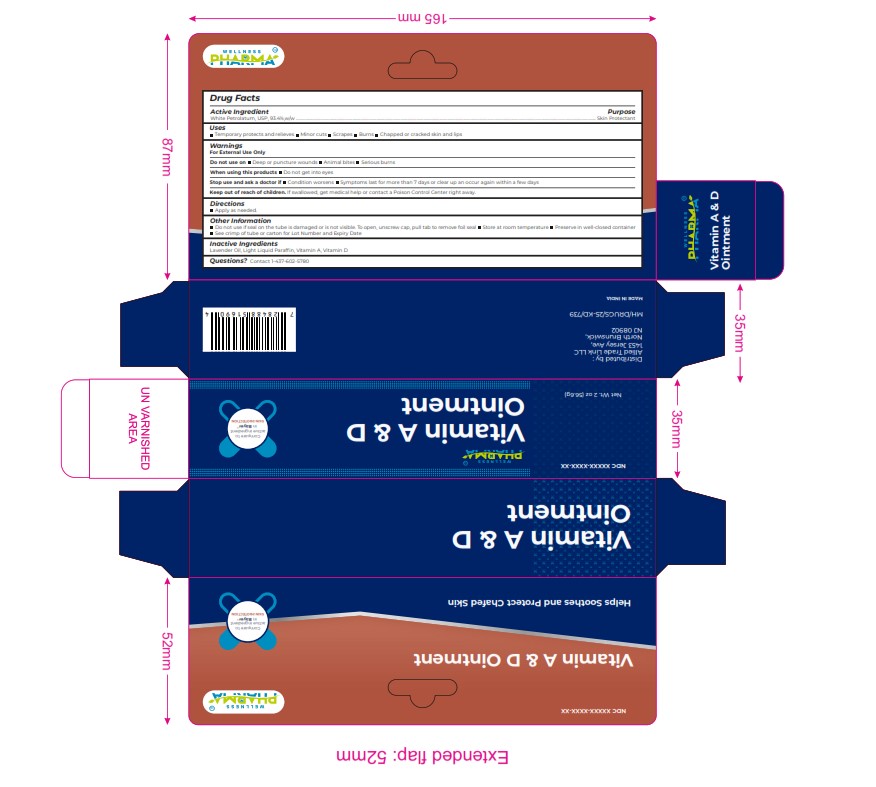 DRUG LABEL: VITAMIN A and D
NDC: 84387-007 | Form: OINTMENT
Manufacturer: ALLIED TRADE LINK LLC
Category: otc | Type: HUMAN OTC DRUG LABEL
Date: 20241113

ACTIVE INGREDIENTS: WHITE PETROLATUM 93.4 g/100 g
INACTIVE INGREDIENTS: PARAFFINUM LIQUIDUM; LAVENDER OIL; VITAMIN D; VITAMIN A

VITAMIN A AND D

DOSAGE AND ADMINISTRATION

White Petrolatum, USP, 93.4%,w/w

Apply as needed.

Warnings
For External Use Only
Do not use on Deep or puncture wounds Animal bites Serious burns
When using this products Do not get into eyes
Stop use and ask a doctor if Condition worsens Symptoms last for more than 7 days or clear up an occur again within a few days
Keep out of reach of children. If swallowed, get medical help or contact a Poison Control Center right away.

Inactive Ingredients
Lavender Oil, Light Liquid Parafﬁn, Vitamin A, Vitamin D

Uses
Temporary protects and relieves Minor cuts Scrapes Burns Chapped or cracked skin and lips

Keep out of reach of children. If swallowed, get medical help or contact a Poison Control Center right away.

PURPOSE

.. Skin Protectant

Warnings
For External Use Only
Do not use on Deep or puncture wounds Animal bites Serious burns
When using this products Do not get into eyes
Stop use and ask a doctor if Condition worsens Symptoms last for more than 7 days or clear up an occur again within a few days
Keep out of reach of children. If swallowed, get medical help or contact a Poison Control Center right away.